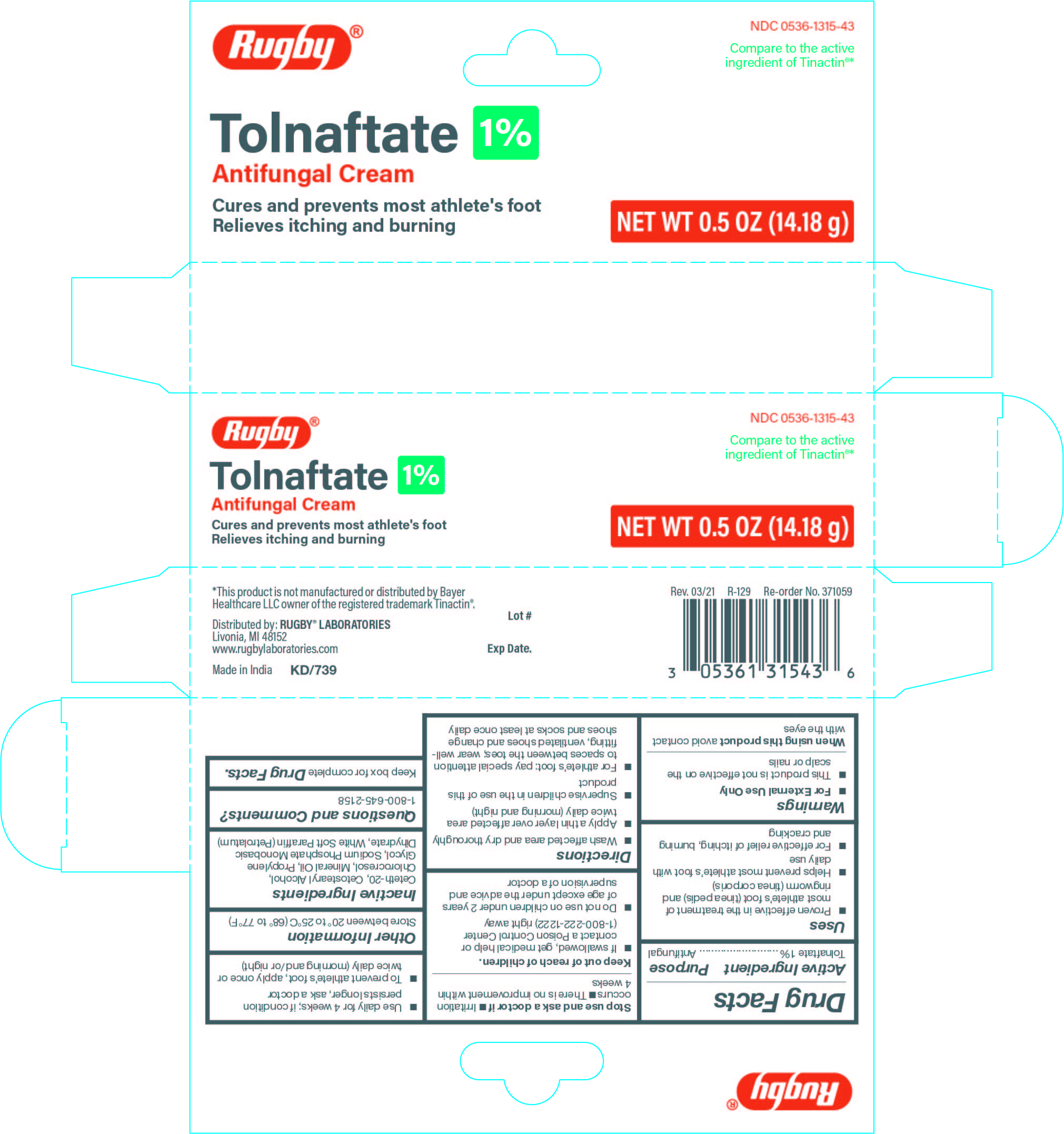 DRUG LABEL: CR-371059 Tolnaftate 1% Cream
NDC: 0536-1315 | Form: CREAM
Manufacturer: Rugby Laboratories
Category: otc | Type: HUMAN OTC DRUG LABEL
Date: 20251125

ACTIVE INGREDIENTS: TOLNAFTATE 1 g/100 g
INACTIVE INGREDIENTS: CETETH-20; MINERAL OIL; CHLOROCRESOL; PROPYLENE GLYCOL; SODIUM PHOSPHATE, MONOBASIC, DIHYDRATE; PETROLATUM; CETOSTEARYL ALCOHOL

CR-371059 Tolnaftate 1% Cream

Active Ingredient

Tolnaftate 1%

Purpose

Antifungal

Uses

• Proven effective in the treatment of most athlete's foot (tinea pedis) and ringworm (tinea corporis)

• Helps prevent most athlete's foot with daily use

• For effective relief of itching, burning, and cracking

Warnings

• For External Use Only

• This product is not effective on the scalp or nails

When using this product

Avoid contact with the eyes

Stop use and ask a doctor if

• Irritation occurs

• There is no improvement within 4 weeks

Keep out of reach of children

• If swallowed, get medical help or contact a Poisen Control Center (1-800-222-1222) right away

• Do not use on children under 2 years of age except under the advice and supervision of a doctor

Directions

• Wash affected area and dry thoroughly

• Apply a thin layer over affected area twice daily (morning and night)

• Supervise children in the use of this product

• For athlete's foot: pay special attention to spaces between the toes; wear well-fitting, ventilated shoes and change shoes and socks

at least once daily

• Use daily for 4 weeks; if condition persists longer, ask a doctor

• To prevent athlete's foot, apply once or twice daily (morning and/or night)

Other Information

Store between 20° to 25ºC (68º to 77ºF)

Inactive Ingredients

Ceteth-20, Cetostearyl Alcohol, Chlorocresol, Mineral Oil, Propylene Glycol, Sodium Phosphate Dihydrate, White Soft Paraffin (Petrolatum)

Questions and Comments?

1-800-645-2158